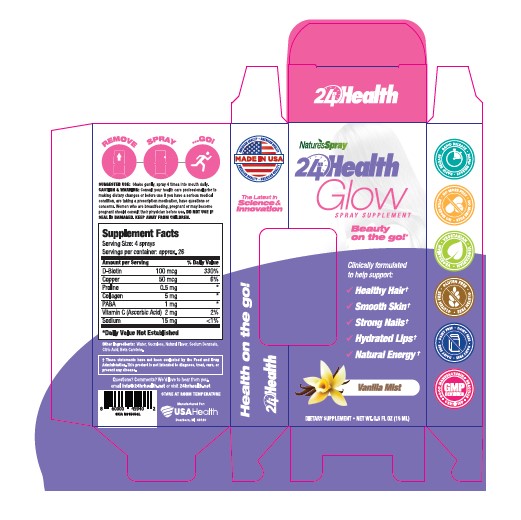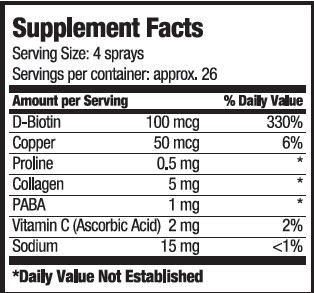 DRUG LABEL: 24hr Health Glow
NDC: 80893-007 | Form: SPRAY
Manufacturer: USA Health
Category: other | Type: Dietary Supplement
Date: 20201106

ACTIVE INGREDIENTS: BIOTIN 100 ug/15 mL; COPPER 50 ug/15 mL; PROLINE .5 mg/15 mL; ASCORBIC ACID 2 mg/15 mL; SODIUM 15 mg/15 mL; AMINOBENZOIC ACID 5 mg/15 mL; COLLAGEN ALPHA-1(I) CHAIN BOVINE 1 mg/15 mL
INACTIVE INGREDIENTS: WATER; SUCRALOSE; SODIUM BENZOATE; CITRIC ACID MONOHYDRATE

24hr Health Glow

Purpose

Clinically formulated to help support:

- Healthy Hair
- Smooth Skin
- Strong Nails
- Hydrated Lips
- Natural Energy

Precautions

Consult your health care professional prior to making dietary changes or before use if you have a serious medical condition, are taking a prescription medicine, have questions or concerns.

Warning

Women who are breastfeeding, pregnant, or may become pregnant should consult their physician before use.

Safe Handling

Do not use if damaged. Keep away from children.

Dosage

Shake gently. Spray 4 times into mouth daily.